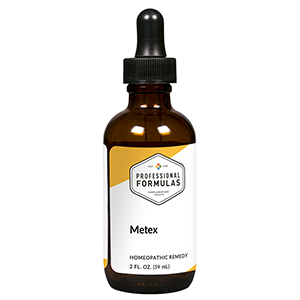 DRUG LABEL: Metex
NDC: 63083-6013 | Form: LIQUID
Manufacturer: Professional Complementary Health Formulas
Category: homeopathic | Type: HUMAN OTC DRUG LABEL
Date: 20190815

ACTIVE INGREDIENTS: PLANTAGO MAJOR WHOLE 3 [hp_X]/59 mL; COPPER 6 [hp_X]/59 mL; LYCOPODIUM CLAVATUM SPORE 6 [hp_X]/59 mL; ALUMINUM OXIDE 30 [hp_X]/59 mL; ARSENIC TRIOXIDE 30 [hp_X]/59 mL; CADMIUM 30 [hp_X]/59 mL; MERCURIUS SOLUBILIS 30 [hp_X]/59 mL; NICKEL SULFATE HEXAHYDRATE 30 [hp_X]/59 mL; LEAD 30 [hp_X]/59 mL; RUBIDIUM 30 [hp_X]/59 mL; STAINLESS STEEL 316L 30 [hp_X]/59 mL; TITANIUM 30 [hp_X]/59 mL
INACTIVE INGREDIENTS: ALCOHOL; WATER

X13

ACTIVE INGREDIENTS

Plantago major 3X
Cuprum metallicum 6X, 30X
Lycopodium clavatum 6X
Alumina 30X
Arsenicum album 30X
Cadmium metallicum 30X
Mercurius solubilis 30X
Niccolum sulphuricum 30X
Plumbum metallicum 30X
Rubidium 30X
Stainless steel 30X
Titanium 30X

QUESTIONS

Professional Formulas

PO Box 2034 Lake Oswego, OR 97035

INDICATIONS

For the temporary relief of occasional headache, weakness or tiredness, minor joint or muscle aches, constipation, nausea or vomiting, or confusion due to sensitivity to or exposure to heavy metals.*

PURPOSE

*Claims based on traditional homeopathic practice, not accepted medical evidence. Not FDA evaluated.

WARNINGS

In case of overdose, get medical help or contact a poison control center right away.

Keep out of the reach of children.

PREGNANCY OR BREAST FEEDING

If pregnant or breastfeeding, ask a healthcare professional before use.

DIRECTIONS

Place drops under tongue 30 minutes before/after meals. Adults and children 12 years and over: Take 10 drops up to 3 times per day. Consult a physician for use in children under 12 years of age.

OTHER INFORMATION

Tamper resistant. If seal is broken, do not use. After opening, close container tightly and store at room temperature away from heat.

INACTIVE INGREDIENTS

20% ethanol, purified water.

LABEL

Est 1985

Professional Formulas

Complementary Health

Metex

Homeopathic Remedy

2 FL. OZ. (59 mL)